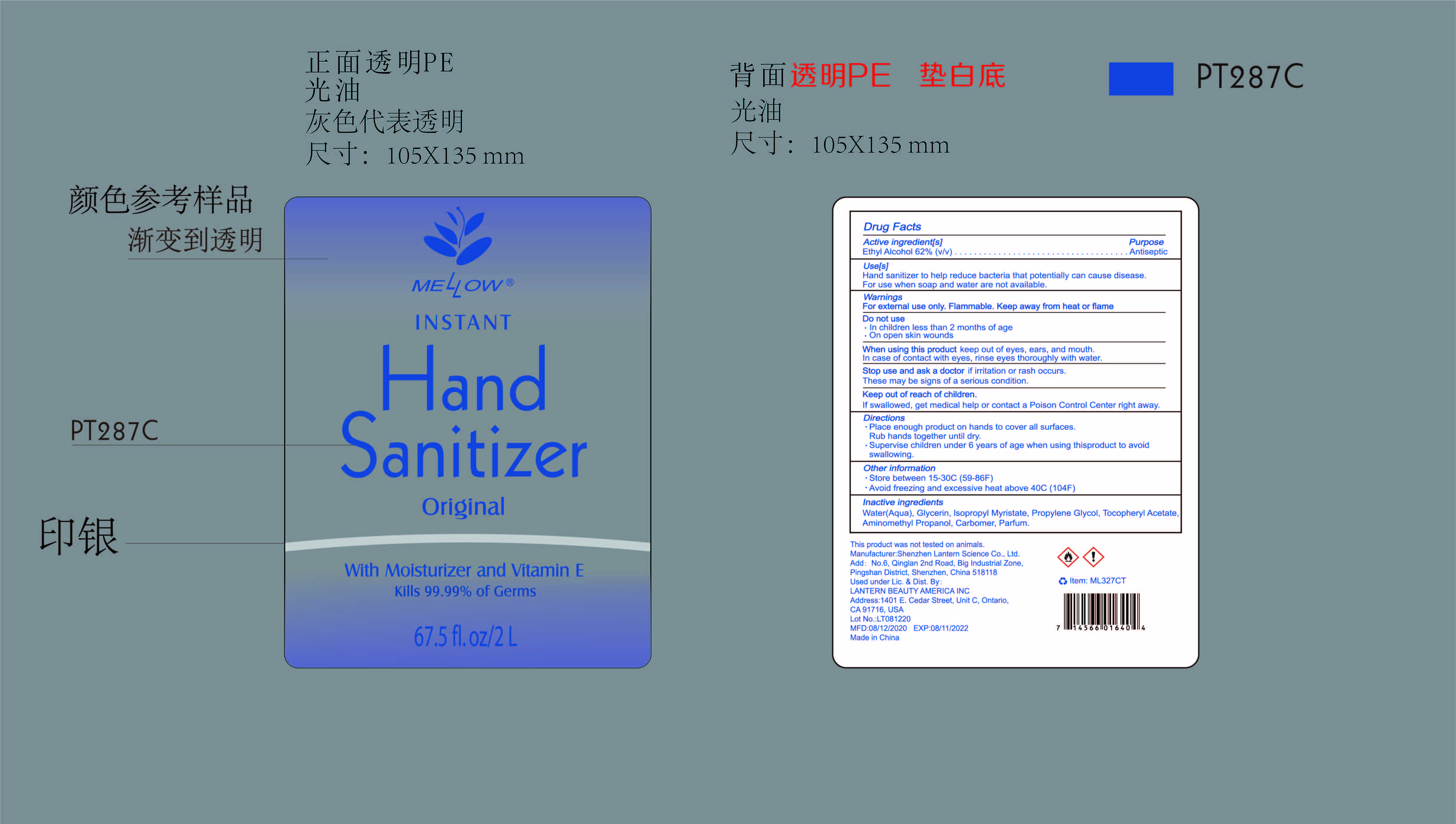 DRUG LABEL: Mellow hand sanitizer original ML327CT
NDC: 54860-305 | Form: LIQUID
Manufacturer: Shenzhen Lantern Scicence Co.,Ltd.
Category: otc | Type: HUMAN OTC DRUG LABEL
Date: 20200804

ACTIVE INGREDIENTS: ALCOHOL 62 mL/100 mL
INACTIVE INGREDIENTS: PROPYLENE GLYCOL 0.01 mL/100 mL; CARBOMER 940 0.26 mL/100 mL; AMINOMETHYLPROPANOL 0.08 mL/100 mL; WATER 37.5648 mL/100 mL; GLYCERIN 0.01 mL/100 mL; LEMON 0.075 mL/100 mL; ISOPROPYL MYRISTATE 0.0001 mL/100 mL; .ALPHA.-TOCOPHEROL ACETATE 0.0001 mL/100 mL

Mellow hand sanitizer original ML327CT

Active Ingredient

Active Ingredient Purpose

Ethyl Alcohol 62%（V/V） Antiseptic

Use

Hand sanitizer helps to reduce bacteria that potentially can cause disease.For use when soap and water are not available.

Use(s)

Hand sanitizer to help reduce bacteria that potentially can cause disease.For use when soap and water are not available.

Warning

For external use only,Flammable,Keep away from heat or flame.

WARNINGS AND PRECAUTIONS

For external use only.

Flammable, keep away from heat and flame.

STOP USE

Discontinue if skin becomes irritated and ask a doctor .

Keep out of reach of children. In case of accidental ingestion, seek professional assistance or contact a poson control center immediately.

keep out of reach of children

If swallowed,get medical help or contact a Poison Control Center right away.

DOSAGE AND ADMINISTRATION

Recommended for repeated use.

use anywhere without water.

Inactive ingredients

Water(Aqua),Glycerin,Isopropyl Myristate,Propylene Glycol,Tocopheryl acetate,Aminomethyl propanol,Carbomer,Fragrance(Parfum).

Directions

place enough product on hands to cover all surfaces,Rub hands together until dry.Supervise children under 6 years of age when using this product to avoid swallowing.

When using this product

keep out of eyes. In case of contact with eyes, flush thoroughly with water.

Do not inhale or ingest.

Avoid contact with broken skin.

Other information

Do not store above 105F.

May discolor some fabrics.

Harmful to wood finishes and plastics.

When using this product

Keep out of eyes,ears,and mouth.In case of contact with eyes.rinse eyes thoroughly with water.

Other information

Store between 15-30C(59-86F).Avoid freezing or excessive heat above 40C(104F)

Stop use and ask a doctor

these may be signs of a serious condition

Purpose

Antiseptic

Do not use

In children less than 2 months of age

On open skin wounds